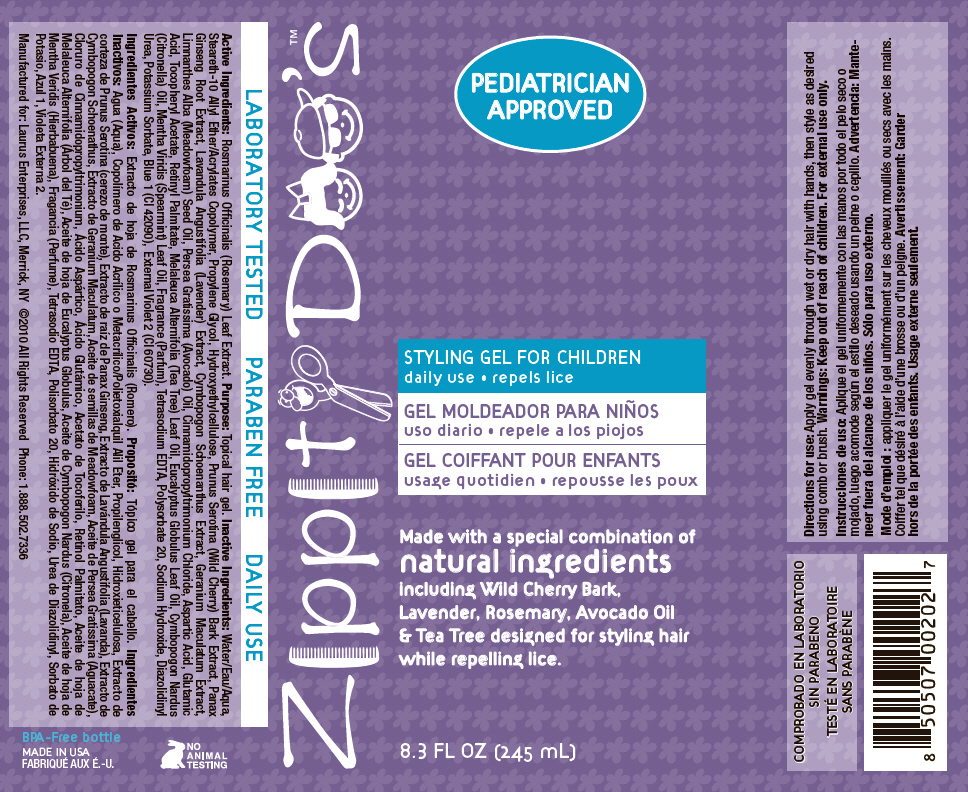 DRUG LABEL: Zippity Doos 
NDC: 57240-2027 | Form: GEL
Manufacturer: Laurus Enterprises, LLC
Category: homeopathic | Type: HUMAN OTC DRUG LABEL
Date: 20130227

ACTIVE INGREDIENTS: Rosemary 0.023 mg/1 mL
INACTIVE INGREDIENTS: Water; Propylene Glycol; Prunus Serotina Bark; Asian Ginseng; Lavandula Angustifolia Flowering Top; Cymbopogon Schoenanthus Top; Geranium Maculatum Root; Meadowfoam Seed Oil; Avocado Oil; Aspartic Acid; Glutamic Acid; .Alpha.-Tocopherol Acetate; Vitamin A Palmitate; Tea Tree Oil; Eucalyptus Oil; Citronella Oil; Spearmint Oil; Edetate Sodium; Polysorbate 20; Sodium Hydroxide; Diazolidinyl Urea; Potassium Sorbate; FD&C Blue No. 1

Zippity Doo's™
STYLING GEL FOR CHILDREN

Active Ingredients

Rosmarinus Officinalis (Rosemary) Leaf Extract.

Purpose

Topical hair gel.

Inactive Ingredients

Water/Eau/Aqua, Steareth-10 Allyl Ether/Acrylates Copolymer, Propylene Glycol, Hydroxyethylcellulose, Prunus Serotina (Wild Cherry) Bark Extract, Panax Ginseng Root Extract, Lavandula Angustifolia (Lavender) Extract, Cymbopogon Schoenanthus Extract, Geranium Maculatum Extract, Limnanthes Alba (Meadowfoam) Seed Oil, Persea Gratissima (Avocado) Oil, Cinnamidopropyltrimonium Chloride, Aspartic Acid, Glutamic Acid, Tocopheryl Acetate, Retinyl Palmitate, Melaleuca Alternifolia (Tea Tree) Leaf Oil, Eucalyptus Globulus Leaf Oil, Cymbopogon Nardus (Citronella) Oil, Mentha Viridis (Spearmint) Leaf Oil, Fragrance (Parfum), Tetrasodium EDTA, Polysorbate 20, Sodium Hydroxide, Diazolidinyl Urea, Potassium Sorbate, Blue 1 (CI 42090), External Violet 2 (CI 60730).

Directions for use

INDICATIONS AND USAGE

Apply gel evenly through wet or dry hair with hands, then style as desired using comb or brush.

Warnings

Keep out of reach of children.

For external use only.

PRINCIPAL DISPLAY PANEL - 245 mL Bottle Label

Zippity Doo's™

PEDIATRICIAN
APPROVED

STYLING GEL FOR CHILDREN

daily use • repels lice

Made with a special combination of
natural ingredients
including Wild Cherry Bark,
Lavender, Rosemary, Avocado Oil
& Tea Tree designed for styling hair
while repelling lice.

8.3 FL OZ (245 mL)